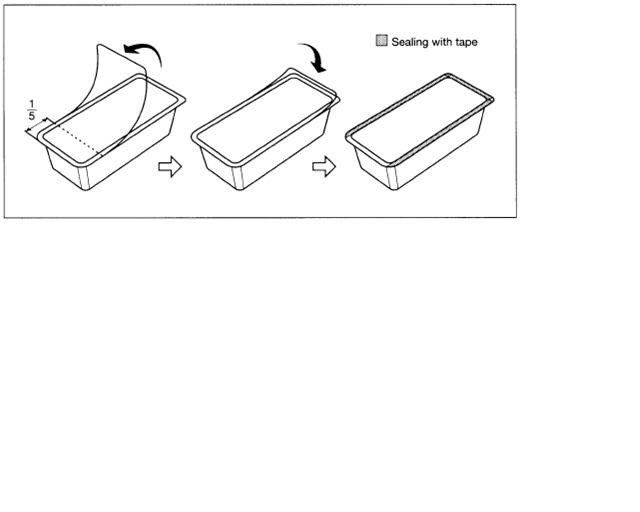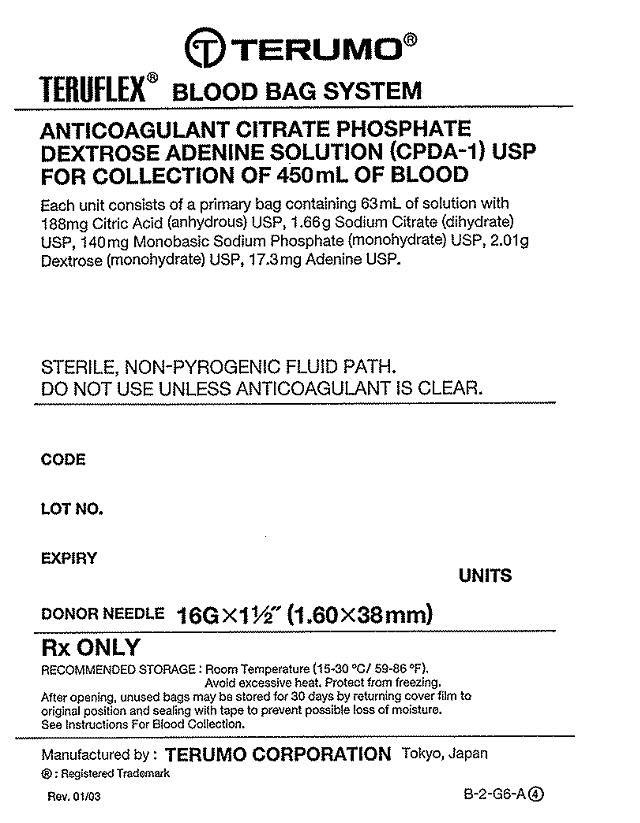 DRUG LABEL: TERUFLEX Blood Bag System Anticoagulant Citrate Phosphate Dextrose Adenine (CPDA-1)
NDC: 53877-001 | Form: SOLUTION
Manufacturer: Terumo Corporation
Category: prescription | Type: HUMAN PRESCRIPTION DRUG LABEL
Date: 20181207

ACTIVE INGREDIENTS: Anhydrous Citric Acid 2.99 g/1000 mL; Trisodium Citrate Dihydrate 26.3 g/1000 mL; SODIUM PHOSPHATE, MONOBASIC, MONOHYDRATE 2.22 g/1000 mL; Dextrose Monohydrate 31.9 g/1000 mL; Adenine 0.275 g/1000 mL
INACTIVE INGREDIENTS: Water

TERUFLEX® BLOOD BAG SYSTEM CPDA-1 SOLUTION For the collection of 450 mL of Whole Blood

INDICATIONS AND USAGE

Revised 2011-11
N-BB-CA-A 5
BB89X505+5
FULL PRESCRIBING INFORMATION
*Sections or subsections omitted from the Full Prescribing Information are not listed [includes sections 4, 6, 7, 8, 9, 10, 12, 13, 14, 15 and 17].
1. INDICATIONS AND USAGE
1.1. Read these instructions carefully before use.
1.2. Rx ONLY
1.3. Intended for the collection, processing and preservation of Whole Blood and blood components. Not intended for direct intravenous infusion.
1.4. For the collection of 450 mL +/- 10% Whole Blood.
1.5. For further processing, use standard component processing techniques.

2. DOSAGE AND ADMINISTRATION

2.1. To open blister package, peel cover film back 4/5 of its length.

2.2. Prepare the blood bag following your institution's standard operating procedures.

2.3. Make a loose knot in the donor tubing approximately 10 cm or 4 inches from the needle unless alternate methods are used to seal the tubing at the end of collection.

2.4. Temporarily clamp donor tubing.

2.5. Suspend the collection bag as far as possible below the donor's arm.

2.6. Apply blood pressure cuff or tourniquet to donor's arm. Disinfect site of phlebotomy. If blood pressure cuff is used, inflate to approximately 60 mmHg.

2.7. Remove needle cover and perform phlebotomy.

2.7.1. CAUTION: Do not touch the needle after removing the needle cover.

2.8. Remove the temporary clamp on the donor tubing to permit blood flow into the collection bag.

2.9. Secure donor tubing to donor's arm.

2.10. Mix blood with anticoagulant in the collection bag and continue to mix at several intervals during collection and immediately after collection. If using an automated mixer, follow manufacturer's instructions.

2.11. Collect labeled volume of blood 450 mL (+/- 10%).

2.12. When the desired amount of blood has been collected, seal the tubing or tighten the loose knot (white knot) prepared in Step 2.3. Temporarily clamp between the knot and needle. Sever donor tubing between knot and clamp. Alternate methods may be used to seal tubing. Collect blood samples using careful attention to aseptic technique and following your institution's standard operating procedures.

2.12.1. CAUTION: Do not use a dielectric tube sealer to seal the tubing while the needle is connected to the donor's body unless it is approved for such a purpose.

2.13. Reapply clamp to donor tubing; release pressure on donor's arm and remove needle. If using a needle safety device, follow manufacturer's instructions.

2.13.1. CAUTION: Discard phlebotomy needle/donor tubing according to institutional procedures.

2.14. Immediately after collection, invert collection bag several times to assure blood and anticoagulant are well mixed.

2.15. Strip blood from donor tubing into collection bag, mix well, and allow tubing to refill; repeat once. Make an appropriate number of segments of anticoagulated blood for testing by sealing on or near X marks. Leave segments attached to Whole Blood unit.

2.16. The time between Whole Blood collection and component separation may vary depending on both the blood bag system and processing options selected. Follow your institution's standard operating procedures to prepare components.

2.16.1. If the Whole Blood is to be processed into room temperature components, maintain the blood at ambient temperature.

2.16.2. If the Whole Blood is to be processed into other components (including Plasma Frozen Within 24 Hours After Phlebotomy), Whole Blood must either be placed in storage at a temperature between 1-6oC within 8 hours of blood collection or cooled towards a temperature between 1-10oC (e.g. during transport) and then placed in storage at a temperature between 1-6oC within 8 hours of blood collection or cooled towards a temperature between 1-10oC (e.g. during transport) and then placed in storage at a temperature between 1-6oC upon arrival at the processing center.

2.17. Platelet Rich Plasma and Platelets should be separated from the Red Blood Cells within 8 hours of blood collection, if prepared.

2.18. Plasma intended for production of Fresh Frozen Plasma should be separated from the Red Blood Cells and placed in a freezer at -18oC or colder within 8 hours of blood collection.

2.19. Plasma intended for production of Plasma Frozen Within 24 Hours After Phlebotomy (PF24) should be placed in a freezer at -18oC or colder within 24 hours of blood collection.

2.20. For further preparation and processing of other plasma components, use standard processing and storage techniques following approved regulations and standards.

2.21. Select the appropriate spin condition and centrifuge Whole Blood unit to separate CPDA-1 Red Blood Cells from plasma or platelet rich plasma, as appropriate.

2.22. Break the CLIKTIP (inline closure device) of primary collection bag and transfer plasma into satellite bag, or transfer platelet rich plasma into XT-612 Platelet Bag. Clamp transfer tubing of satellite bag.

2.23. Seal tubing of primary bag in two places, cut between seals, and if applicable, separate from satellite bag(s).

2.24. Store CPDA-1 Red Blood Cells (or Whole Blood) between 1-6oC for up to 35 days.

2.25. If prepared, store Platelets between 20-24oC for up to 5 days in XT-612 bag.

3. DOSAGE FORMS AND STRENGTHS

3.1. 63 mL Citrate Phosphate Dextrose Adenine (CPDA-1) anticoagulant USP for collection of 450 mL Whole Blood. Each 63 mL contains 188 mg Citric Acid (anhydrous) USP, 1.66 g Sodium Citrate (dihydrate) USP, 140 mg Monobasic Sodium Phosphate (monohydrate) USP, 2.01 g Dextrose (monohydrate) USP and 17.3 mg Adenine USP.

5. WARNINGS AND PRECAUTIONS

5.1. Rx ONLY

5.2. Do not use unless solutions are clear and free from particulates.

5.3. Always inspect the blood bag set for leaks before use.

5.4. Avoid excessive heat and direct sunlight. Protect from freezing.

5.5. Recommended storage conditions: Room Temperature (15-30oC/59-86oF)

5.6. It is normal to have condensation in the blister packaging. If the amount of moisture is greater than expected, check for leaks from the fluid-filled components of the blood bag set.

5.7. Use aseptic techniques.

5.8. Do not use a dielectric tube sealer to seal the tubing while the needle is connected to the donor's body unless it is approved for such a purpose.

5.9. Do not touch needle after removing the needle cover.

5.10. Discard phlebotomy needle/donor tubing according to institutional procedures.

5.11. The AGELESS (oxygen absorber packet, Mitsubishi Gas Chemical) contained in this package absorbs oxygen and generates heat on removal. Do not open and handle it with care.

5.12. Dispose of the AGELESS packet with the blister tray.

5.13. Do not dispose the AGELESS packet with wastes containing volatile or flammable materials.

5.14. Due to possible exposure to infectious agents in the handling of blood, take adequate precautions at all times to prevent exposure to and transmission of such agents. Follow your institution's standard operating procedures.

11. DESCRIPTION

11.1. This blood bag system includes a 16 gauge x 1 1/2 inch (1.60 x 38 mm) needle with needle cover and a 450 mL (nominal capacity 600 mL) primary collection bag containing 63 mL Citrate Phosphate Dextrose Adenine (CPDA-1) anticoagulant. The Double blood bag set has one integrally attached empty satellite bag (nominal capacity 400 mL). The Triple blood bag set has one integrally attached empty satellite bag (nominal capacity 400 mL) and one empty XT-612 5 day Platelet bag (nominal capacity 500 mL).

11.2. The blood bag collection set is made of PVC (polyvinyl chloride with DEHP plasticizer).

11.3. The blood bag has no components made of natural rubber latex.

11.4. Tubing internal diameter (ID) nominal 3.0 mm.

11.5. Tubing outer diameter (OD) nominal 4.4 mm.

11.6. Donor tubing line maximum 19 segments available.

16. HOW SUPPLIED/STORAGE AND HANDLING

16.1. Single use only.

16.2. Sterile and non-pyrogenic fluid path. Sterilized by steam. Opacity of the blood bag system may be observed. This is due to moisture absorption during the sterilization process. This is normal and does not affect the solution quality or safety. The opacity will diminish gradually.

16.3. A Material Safety Data Sheet (MSDS) is not required for this product.

16.4. Recommended storage conditions: Room Temperature (15-30oC/59-86oF)

16.5. Avoid excessive heat and direct sunlight. Protect from freezing.

16.6. To open blister package, peel cover film back 4/5 of its length.

16.7. After opening the blister package unused blood bags may be stored at room temperature for 96 hours or they may be stored for 30 days by returning cover film to original position and sealing with tape to prevent possible evaporation of solutions.
16.8. Blood bags in the unopened blister package may be used through the last day of the month and year as indicated on the original manufacturer's packaging.
16.9. The AGELESS packet contained in this package absorbs oxygen and generates heat on removal. Do not open and handle it with care.
16.10. Dispose of the AGELESS packet with the blister tray.
16.11. Do not dispose the AGELESS packet with wastes containing volatile or flammable materials.
16.12. For the Single blood bag set, Code BB*SCD456A, is supplied 60/case.
16.13. For the Double blood bag set, BB*DCD456A, is supplied 30/case.
16.14. For the Triple blood bag set, BB*TCD456A is supplied 30/case.
MANUFACTURED BY: TERUMO CORPORATION
44-1, 2-CHOME, HATAGAYA, SHIBUYA-KU, TOKYO, 151-0072, JAPAN
MADE IN JAPAN
®: Registered Trademark
(c) TERUMO CORPORATION November, 2011 11K08
AGELESS is a registered trademark of MITSUBISHI GAS CHEMICAL CO., INC.

Tray/Case Label
TERUFLEX® BLOOD BAG SYSTEM
ANTICOAGULANT CITRATE PHOSPHATE
DEXTROSE ADENINE SOLUTION (CPDA-1) USP
FOR COLLECTION OF 450mL OF BLOOD
Each unit consists of a primary bag containing 63 mL of solution with
188 mg Citric Acid (anhydrous) USP, 1.66 g Sodium Citrate (dihydrate)
USP, 140 mg Monobasic Sodium Phosphate (monohydrate) USP, 2.01 g
Dextrose (monohydrate) USP, 17.3 mg Adenine USP.
STERILE, NON-PYROGENIC FLUID PATH.
DO NOT USE UNLESS ANTICOAGULANT IS CLEAR
CODE
LOT NO.
EXPIRY
UNITS
DONOR NEEDLE 16G x 1 1/2˝ (1.60 x 38mm)
Rx ONLY
RECOMMENDED STORAGE: Room Temperature (15-30°C/59-86°F).
Avoid excessive heat. Protect from freezing.
After opening, unused bags may be stored for 30 days by returning cover film to
original position and sealing with tape to prevent possible loss of moisture.
See Instructions For Blood Collection.
Manufactured by : TERUMO CORPORATION Tokyo, Japan
® : Registered Trademark
Rev. 01/03